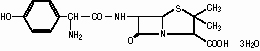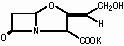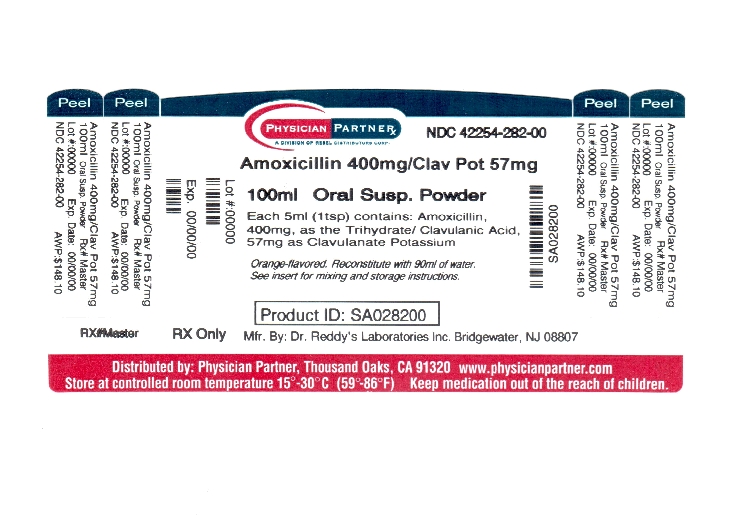 DRUG LABEL: Amoxicillin and Clavulanate Potassium
NDC: 42254-282 | Form: POWDER, FOR SUSPENSION
Manufacturer: Rebel Distributors Corp
Category: prescription | Type: HUMAN PRESCRIPTION DRUG LABEL
Date: 20120828

ACTIVE INGREDIENTS: AMOXICILLIN 400 mg/5 mL; CLAVULANATE POTASSIUM 57 mg/5 mL
INACTIVE INGREDIENTS: SILICON DIOXIDE; XANTHAN GUM; ASPARTAME; HYPROMELLOSES; MANNITOL; SACCHARIN SODIUM DIHYDRATE

Amoxicillin and Clavulanate Potassium
Powder for Oral Suspension and Chewable Tablets

Rx Only
Issued: November 2011

To reduce the development of drug-resistant bacteria and maintain the effectiveness of Amoxicillin and Clavulanate Potassium and other antibacterial drugs, Amoxicillin and Clavulanate Potassium should be used only to treat or prevent infections that are proven or strongly suspected to be caused by bacteria.

DESCRIPTION

Amoxicillin and Clavulanate Potassium is an oral antibacterial combination consisting of the semisynthetic antibiotic amoxicillin and the β-lactamase inhibitor, clavulanate potassium (the potassium salt of clavulanic acid). Amoxicillin is an analog of ampicillin, derived from the basic penicillin nucleus, 6-aminopenicillanic acid. The amoxicillin molecular formula is C16H19N3O5S•3H2O, and the molecular weight is 419.46. Chemically, amoxicillin is (2S,5R,6R)-6-[(R)-(-)-2-Amino-2-(p-hydroxyphenyl)acetamido]-3,3-dimethyl-7-oxo-4-thia-1-azabicyclo[3.2.0]heptane-2-carboxylic acid trihydrate and may be represented structurally as:

Clavulanic acid is produced by the fermentation of Streptomyces clavuligerus. It is a β-lactam structurally related to the penicillins and possesses the ability to inactivate a wide variety of β-lactamases by blocking the active sites of these enzymes. Clavulanic acid is particularly active against the clinically important plasmid-mediated β-lactamases frequently responsible for transferred drug resistance to penicillins and cephalosporins. The clavulanate potassium molecular formula is C8H8KNO5, and the molecular weight is 237.25. Chemically, clavulanate potassium is potassium (Z)-(2R,5R)-3-(2-hydroxyethylidene)-7-oxo-4-oxa-1-azabicyclo[3.2.0]-heptane-2-carboxylate and may be represented structurally as:

Inactive Ingredients:

Powder for Oral Suspension—Colloidal silicon dioxide, flavorings (see HOW SUPPLIED), xanthan gum, and 1 or more of the following: Aspartamea, hypromellose, mannitol, silica gel, silicon dioxide, and sodium saccharin. Chewable Tablets—Colloidal silicon dioxide, flavorings (see HOW SUPPLIED), magnesium stearate, mannitol, and 1 or more of the following: Aspartamea, D&C Yellow No. 10, FD&C Red No. 40, glycine, sodium saccharin and succinic acid.

a See PRECAUTIONS—Information for the Patient.

Each 125 mg/31.25 mg chewable tablet and each 5 mL of reconstituted 125 mg/31.25 mg per 5 mL oral suspension of Amoxicillin and Clavulanate Potassium contains 0.16 mEq potassium. Each 250 mg/62.5 mg chewable tablet and each 5 mL of reconstituted 250 mg/62.5 mg per 5 mL oral suspension of Amoxicillin and Clavulanate Potassium contains 0.32 mEq potassium. Each 200 mg/28.5 mg chewable tablet and each 5 mL of reconstituted 200 mg/28.5 mg per 5 mL oral suspension of Amoxicillin and Clavulanate Potassium contains 0.14 mEq potassium. Each 400 mg/57 mg chewable tablet and each 5 mL of reconstituted 400 mg/57 mg per 5 mL oral suspension of Amoxicillin and Clavulanate Potassium contains 0.29 mEq of potassium.

CLINICAL PHARMACOLOGY

Amoxicillin and clavulanate potassium are well absorbed from the gastrointestinal tract after oral administration of Amoxicillin and Clavulanate Potassium. Dosing in the fasted or fed state has minimal effect on the pharmacokinetics of amoxicillin. While Amoxicillin and Clavulanate Potassium can be given without regard to meals, absorption of clavulanate potassium when taken with food is greater relative to the fasted state. In 1 study, the relative bioavailability of clavulanate was reduced when Amoxicillin and Clavulanate Potassium was dosed at 30 and 150 minutes after the start of a high-fat breakfast. The safety and efficacy of Amoxicillin and Clavulanate Potassium have been established in clinical trials where Amoxicillin and Clavulanate Potassium was taken without regard to meals.

Oral administration of single doses of 400 mg/57 mg chewable tablets of Amoxicillin and Clavulanate Potassium and 400 mg/57 mg per 5 mL suspension to 28 adult volunteers yielded comparable pharmacokinetic data:

Dosea | AUC0-∞ (mcg.hr/mL) |  | Cmax (mcg/mL)b
(amoxicillin/ clavulanate potassium) | amoxicillin; (±S.D.) | clavulanate potassium; (±S.D.) | amoxicillin (±S.D.) | clavulanate potassium (±S.D.)
400/57 mg; (5 mL of suspension) | 17.29 ± 2.28 | 2.34 ± 0.94 | 6.94 ± 1.24 | 1.10 ± 0.42
400/57 mg; (1 chewable tablet) | 17.24 ± 2.64 | 2.17 ± 0.73 | 6.67 ± 1.37 | 1.03 ± 0.33

a Administered at the start of a light meal.

b Mean values of 28 normal volunteers. Peak concentrations occurred approximately 1 hour after the dose.

Oral administration of 5 mL of 250 mg/62.5 mg per 5 mL suspension of Amoxicillin and Clavulanate Potassium or the equivalent dose of 10 mL of 125 mg/31.25 mg per 5 mL suspension of Amoxicillin and Clavulanate Potassium provides average peak serum concentrations approximately 1 hour after dosing of 6.9 mcg/mL for amoxicillin and 1.6 mcg/mL for clavulanic acid. The areas under the serum concentration curves obtained during the first 4 hours after dosing were 12.6 mcg.hr/mL for amoxicillin and 2.9 mcg.hr/mL for clavulanic acid when 5 mL of 250 mg/62.5 mg per 5 mL suspension of Amoxicillin and Clavulanate Potassium or equivalent dose of 10 mL of 125 mg/31.25 mg per 5 mL suspension of Amoxicillin and Clavulanate Potassium was administered to adult volunteers. One 250 mg/62.5 mg chewable tablet of Amoxicillin and Clavulanate Potassium or two 125 mg/31.25 mg chewable tablets of Amoxicillin and Clavulanate Potassium are equivalent to 5 mL of 250 mg/62.5 mg per 5 mL suspension of Amoxicillin and Clavulanate Potassium and provide similar serum levels of amoxicillin and clavulanic acid.

Amoxicillin serum concentrations achieved with Amoxicillin and Clavulanate Potassium are similar to those produced by the oral administration of equivalent doses of amoxicillin alone. The half-life of amoxicillin after the oral administration of Amoxicillin and Clavulanate Potassium is 1.3 hours and that of clavulanic acid is 1.0 hour. Time above the minimum inhibitory concentration of 1.0 mcg/mL for amoxicillin has been shown to be similar after corresponding every 12 hours and every 8 hours dosing regimens of Amoxicillin and Clavulanate Potassium in adults and children.

Approximately 50% to 70% of the amoxicillin and approximately 25% to 40% of the clavulanic acid are excreted unchanged in urine during the first 6 hours after administration of 10 mL of 250 mg/62.5 mg per 5 mL suspension of Amoxicillin and Clavulanate Potassium.

Concurrent administration of probenecid delays amoxicillin excretion but does not delay renal excretion of clavulanic acid.

Neither component in Amoxicillin and Clavulanate Potassium is highly protein-bound; clavulanic acid has been found to be approximately 25% bound to human serum and amoxicillin approximately 18% bound.

Amoxicillin diffuses readily into most body tissues and fluids with the exception of the brain and spinal fluid. The results of experiments involving the administration of clavulanic acid to animals suggest that this compound, like amoxicillin, is well distributed in body tissues.

Two hours after oral administration of a single 35 mg/kg dose of suspension of Amoxicillin and Clavulanate Potassium to fasting children, average concentrations of 3.0 mcg/mL of amoxicillin and 0.5 mcg/mL of clavulanic acid were detected in middle ear effusions.

Microbiology:

Amoxicillin is a semisynthetic antibiotic with a broad spectrum of bactericidal activity against many gram-positive and gram-negative microorganisms. Amoxicillin is, however, susceptible to degradation by β-lactamases, and therefore, the spectrum of activity does not include organisms which produce these enzymes. Clavulanic acid is a β-lactam, structurally related to the penicillins, which possesses the ability to inactivate a wide range of β-lactamase enzymes commonly found in microorganisms resistant to penicillins and cephalosporins. In particular, it has good activity against the clinically important plasmid-mediated β-lactamases frequently responsible for transferred drug resistance.

The formulation of amoxicillin and clavulanic acid in Amoxicillin and Clavulanate Potassium protects amoxicillin from degradation by β-lactamase enzymes and effectively extends the antibiotic spectrum of amoxicillin to include many bacteria normally resistant to amoxicillin and other β-lactam antibiotics. Thus, Amoxicillin and Clavulanate Potassium possesses the distinctive properties of a broad-spectrum antibiotic and a β-lactamase inhibitor.

Amoxicillin/clavulanic acid has been shown to be active against most strains of the following microorganisms, both in vitro and in clinical infections as described in INDICATIONS AND USAGE.

Gram-Positive Aerobes:

Staphylococcus aureus (β-lactamase and non−β-lactamase−producing)c

c Staphylococci which are resistant to methicillin/oxacillin must be considered resistant to amoxicillin/clavulanic acid.

Gram-Negative Aerobes:

Enterobacter species (Although most strains of Enterobacter species are resistant in vitro, clinical efficacy has been demonstrated with Amoxicillin and Clavulanate Potassium in urinary tract infections caused by these organisms.)

Escherichia coli (β-lactamase and non−β-lactamase−producing)

Haemophilus influenzae (β-lactamase and non−β-lactamase−producing)

Klebsiella species (All known strains are β-lactamase−producing.)

Moraxella catarrhalis (β-lactamase and non−β-lactamase−producing)

The following in vitro data are available, but their clinical significance is unknown.

Amoxicillin/clavulanic acid exhibits in vitro minimal inhibitory concentrations (MICs) of 2 mcg/mL or less against most (≥ 90%) strains of Streptococcus pneumoniaed; MICs of 0.06 mcg/mL or less against most (≥ 90%) strains of Neisseria gonorrhoeae; MICs of 4 mcg/mL or less against most (≥ 90%) strains of staphylococci and anaerobic bacteria; MICs of 8 mcg/mL or less against most (≥ 90%) strains of other listed organisms. However, with the exception of organisms shown to respond to amoxicillin alone, the safety and effectiveness of amoxicillin/clavulanic acid in treating clinical infections due to these microorganisms have not been established in adequate and well-controlled clinical trials.

d Because amoxicillin has greater in vitro activity against S. pneumoniae than does ampicillin or penicillin, the majority of S. pneumoniae strains with intermediate susceptibility to ampicillin or penicillin are fully susceptible to amoxicillin.

Gram-Positive Aerobes:

Enterococcus faecalise

Staphylococcus epidermidis (β-lactamase and non−β-lactamase−producing)

Staphylococcus saprophyticus (β-lactamase and non−β-lactamase−producing)

Streptococcus pneumoniaee, f

Streptococcus pyogenese, f

viridans group Streptococcuse, f

Gram-Negative Aerobes:

Eikenella corrodens (β-lactamase and non−β-lactamase−producing)

Neisseria gonorrhoeaee (β-lactamase and non−β-lactamase−producing)

Proteus mirabilise (β-lactamase and non−β-lactamase−producing)

Anaerobic Bacteria:

Bacteroides species, including Bacteroides fragilis (β-lactamase and non−β-lactamase−producing)

Fusobacterium species (β-lactamase and non−β-lactamase−producing)

Peptostreptococcus speciesf

e Adequate and well-controlled clinical trials have established the effectiveness of amoxicillin alone in treating certain clinical infections due to these organisms.

f These are non−β-lactamase−producing organisms, and therefore, are susceptible to amoxicillin alone.

Susceptibility Testing:

Dilution Techniques:

Quantitative methods are used to determine antimicrobial MICs. These MICs provide estimates of the susceptibility of bacteria to antimicrobial compounds. The MICs should be determined using a standardized procedure. Standardized procedures are based on a dilution method^1 (broth or agar) or equivalent with standardized inoculum concentrations and standardized concentrations of amoxicillin/clavulanate potassium powder.

The recommended dilution pattern utilizes a constant amoxicillin/clavulanate potassium ratio of 2 to 1 in all tubes with varying amounts of amoxicillin. MICs are expressed in terms of the amoxicillin concentration in the presence of clavulanic acid at a constant 2 parts amoxicillin to 1 part clavulanic acid. The MIC values should be interpreted according to the following criteria:
INTERPRETIVE CRITERIA FOR AMOXICILLIN/CLAVULANIC ACID SUSCEPTIBILITY TESTING

For Gram-Negative Enteric Aerobes:

MIC (mcg/mL) | Interpretation
≤ 8/4 | Susceptible (S)
16/8 | Intermediate (I)
≥ 32/16 | Resistant (R)

For Staphylococcus aureusg and Haemophilus influenzae:

MIC (mcg/mL) | Interpretation
≤ 4/2 | Susceptible (S)
≥ 8/4 | Resistant (R)

g Staphylococci which are susceptible to amoxicillin/clavulanic acid but resistant to methicillin/oxacillin must be considered as resistant.

For S. pneumoniae from non-meningitis sources:

Isolates should be tested using amoxicillin/clavulanic acid and the following criteria should be used:

MIC (mcg/mL) | Interpretation
≤ 2/1 | Susceptible (S)
4/2 | Intermediate (I)
≥ 8/4 | Resistant (R)

Note: These interpretive criteria are based on the recommended doses for respiratory tract infections.

A report of “Susceptible” indicates that the pathogen is likely to be inhibited if the antimicrobial compound in the blood reaches the concentration usually achievable. A report of “Intermediate” indicates that the result should be considered equivocal, and, if the microorganism is not fully susceptible to alternative, clinically feasible drugs, the test should be repeated. This category implies possible clinical applicability in body sites where the drug is physiologically concentrated or in situations where high dosage of drug can be used. This category also provides a buffer zone that prevents small uncontrolled technical factors from causing major discrepancies in interpretation. A report of “Resistant” indicates that the pathogen is not likely to be inhibited if the antimicrobial compound in the blood reaches the concentrations usually achievable; other therapy should be selected.

Standardized susceptibility test procedures require the use of laboratory control microorganisms to control the technical aspects of the laboratory procedures. Standard amoxicillin/clavulanate potassium powder should provide the following MIC values:

Microorganism | MIC Range (mcg/mL)h
E. coli ATCC 25922 | 2 to 8
E. coli ATCC 35218 | 4 to 16
H. influenzae ATCC 49247 | 2 to 16
S. aureus ATCC 29213 | 0.12 to 0.5
S. pneumoniae ATCC 49619 | 0.03 to 0.12

h Expressed as concentration of amoxicillin in the presence of clavulanic acid at a constant 2 parts amoxicillin to 1 part clavulanic acid.

Diffusion Techniques:

Quantitative methods that require measurement of zone diameters also provide reproducible estimates of the susceptibility of bacteria to antimicrobial compounds. One such standardized procedure^2 requires the use of standardized inoculum concentrations. This procedure uses paper disks impregnated with 30 mcg of amoxicillin/clavulanate potassium (20 mcg amoxicillin plus 10 mcg clavulanate potassium) to test the susceptibility of microorganisms to amoxicillin/clavulanic acid.

Reports from the laboratory providing results of the standard single-disk susceptibility test with a 30-mcg amoxicillin/clavulanate potassium (20 mcg amoxicillin plus 10 mcg clavulanate potassium) disk should be interpreted according to the following criteria:
INTERPRETIVE CRITERIA FOR AMOXICILLIN/CLAVULANIC ACID SUSCEPTIBILITY TESTING

For Gram-Negative Enteric Aerobes:

Zone Diameter (mm) | Interpretation
≥ 18 | Susceptible (S)
14 to 17 | Intermediate (I)
≤ 13 | Resistant (R)

For Staphylococcus aureusi and Haemophilus influenzaej:

Zone Diameter (mm) | Interpretation
≥ 20 | Susceptible (S)
≤ 19 | Resistant (R)

i Staphylococcus aureus which are resistant to methicillin/oxacillin must be considered as resistant to amoxicillin/clavulanic acid.

j A broth microdilution method should be used for testing Haemophilus influenzae. Betalactamase−negative, ampicillin-resistant strains must be considered resistant to amoxicillin/clavulanic acid.

Interpretation should be as stated above for results using dilution techniques. Interpretation involves correlation of the diameter obtained in the disk test with the MIC for amoxicillin/clavulanic acid.

As with standardized dilution techniques, diffusion methods require the use of laboratory control microorganisms that are used to control the technical aspects of the laboratory procedures. For the diffusion technique, the 30-mcg amoxicillin/clavulanate potassium (20 mcg amoxicillin plus 10 mcg clavulanate potassium) disk should provide the following zone diameters in these laboratory quality control strains:

Microorganism | Zone Diameter (mm)
E. coli ATCC 25922 | 18 to 24 mm
E. coli ATCC 35218 | 17 to 22 mm
S. aureus ATCC 25923 | 28 to 36 mm
Haemophilus influenza ATCC 49247 | 15 to 23 mm

INDICATIONS AND USAGE

Amoxicillin and Clavulanate Potassium is indicated in the treatment of infections caused by susceptible strains of the designated organisms in the conditions listed below:

Lower Respiratory Tract Infections − caused by β-lactamase−producing strains of H. influenzae and M. catarrhalis.

Otitis Media − caused by β-lactamase−producing strains of H. influenzae and M. catarrhalis.

Sinusitis − caused by β-lactamase−producing strains of H. influenzae and M. catarrhalis.

Skin and Skin Structure Infections − caused by β-lactamase−producing strains of S. aureus, E. coli, and Klebsiella spp.

Urinary Tract Infections − caused by β-lactamase−producing strains of E. coli, Klebsiella spp. and Enterobacter spp.

While Amoxicillin and Clavulanate Potassium is indicated only for the conditions listed above, infections caused by ampicillin-susceptible organisms are also amenable to treatment with Amoxicillin and Clavulanate Potassium due to its amoxicillin content. Therefore, mixed infections caused by ampicillin-susceptible organisms and β-lactamase−producing organisms susceptible to Amoxicillin and Clavulanate Potassium should not require the addition of another antibiotic. Because amoxicillin has greater in vitro activity against S. pneumoniae than does ampicillin or penicillin, the majority of S. pneumoniae strains with intermediate susceptibility to ampicillin or penicillin are fully susceptible to amoxicillin and Amoxicillin and Clavulanate Potassium. (See Microbiology.)

To reduce the development of drug-resistant bacteria and maintain the effectiveness of Amoxicillin and Clavulanate Potassium and other antibacterial drugs, Amoxicillin and Clavulanate Potassium should be used only to treat or prevent infections that are proven or strongly suspected to be caused by susceptible bacteria. When culture and susceptibility information are available, they should be considered in selecting or modifying antibacterial therapy. In the absence of such data, local epidemiology and susceptibility patterns may contribute to the empiric selection of therapy.

Bacteriological studies, to determine the causative organisms and their susceptibility to Amoxicillin and Clavulanate Potassium, should be performed together with any indicated surgical procedures.

CONTRAINDICATIONS

Amoxicillin and Clavulanate Potassium is contraindicated in patients with a history of allergic reactions to any penicillin. It is also contraindicated in patients with a previous history of cholestatic jaundice/hepatic dysfunction associated with Amoxicillin and Clavulanate Potassium.

WARNINGS

SERIOUS AND OCCASIONALLY FATAL HYPERSENSITIVITY (ANAPHYLACTIC) REACTIONS HAVE BEEN REPORTED IN PATIENTS ON PENICILLIN THERAPY. THESE REACTIONS ARE MORE LIKELY TO OCCUR IN INDIVIDUALS WITH A HISTORY OF PENICILLIN HYPERSENSITIVITY AND/OR A HISTORY OF SENSITIVITY TO MULTIPLE ALLERGENS. THERE HAVE BEEN REPORTS OF INDIVIDUALS WITH A HISTORY OF PENICILLIN HYPERSENSITIVITY WHO HAVE EXPERIENCED SEVERE REACTIONS WHEN TREATED WITH CEPHALOSPORINS. BEFORE INITIATING THERAPY WITH AMOXICILLIN AND CLAVULANATE POTASSIUM, CAREFUL INQUIRY SHOULD BE MADE CONCERNING PREVIOUS HYPERSENSITIVITY REACTIONS TO PENICILLINS, CEPHALOSPORINS, OR OTHER ALLERGENS. IF AN ALLERGIC REACTION OCCURS, AMOXICILLIN AND CLAVULANATE POTASSIUM SHOULD BE DISCONTINUED AND THE APPROPRIATE THERAPY INSTITUTED. SERIOUS ANAPHYLACTIC REACTIONS REQUIRE IMMEDIATE EMERGENCY TREATMENT WITH EPINEPHRINE. OXYGEN, INTRAVENOUS STEROIDS, AND AIRWAY MANAGEMENT, INCLUDING INTUBATION, SHOULD ALSO BE ADMINISTERED AS INDICATED.

Clostridium difficile associated diarrhea (CDAD) has been reported with use of nearly all antibacterial agents, including Amoxicillin and Clavulanate Potassium, and may range in severity from mild diarrhea to fatal colitis. Treatment with antibacterial agents alters the normal flora of the colon leading to overgrowth of C. difficile.

C. difficile produces toxins A and B which contribute to the development of CDAD. Hypertoxin producing strains of C. difficile cause increased morbidity and mortality, as these infections can be refractory to antimicrobial therapy and may require colectomy. CDAD must be considered in all patients who present with diarrhea following antibiotic use. Careful medical history is necessary since CDAD has been reported to occur over two months after the administration of antibacterial agents.

If CDAD is suspected or confirmed, ongoing antibiotic use not directed against C. difficile may need to be discontinued. Appropriate fluid and electrolyte management, protein supplementation, antibiotic treatment of C. difficile, and surgical evaluation should be instituted as clinically indicated.

Amoxicillin and Clavulanate Potassium should be used with caution in patients with evidence of hepatic dysfunction. Hepatic toxicity associated with the use of Amoxicillin and Clavulanate Potassium is usually reversible. On rare occasions, deaths have been reported (less than 1 death reported per estimated 4 million prescriptions worldwide). These have generally been cases associated with serious underlying diseases or concomitant medications. (See CONTRAINDICATIONS and ADVERSE REACTIONS—Liver.)

PRECAUTIONS

General:

While Amoxicillin and Clavulanate Potassium possesses the characteristic low toxicity of the penicillin group of antibiotics, periodic assessment of organ system functions, including renal, hepatic, and hematopoietic function, is advisable during prolonged therapy.

A high percentage of patients with mononucleosis who receive ampicillin develop an erythematous skin rash. Thus, ampicillin-class antibiotics should not be administered to patients with mononucleosis.

The possibility of superinfections with mycotic or bacterial pathogens should be kept in mind during therapy. If superinfections occur (usually involving Pseudomonas or Candida), the drug should be discontinued and/or appropriate therapy instituted.

Prescribing Amoxicillin and Clavulanate Potassium in the absence of a proven or strongly suspected bacterial infection or a prophylactic indication is unlikely to provide benefit to the patient and increases the risk of the development of drug-resistant bacteria.

Information for the Patient:

Amoxicillin and Clavulanate Potassium may be taken every 8 hours or every 12 hours, depending on the strength of the product prescribed. Each dose should be taken with a meal or snack to reduce the possibility of gastrointestinal upset. Many antibiotics can cause diarrhea. If diarrhea is severe or lasts more than 2 or 3 days, call your doctor.

Diarrhea is a common problem caused by antibiotics which usually ends when the antibiotic is discontinued. Sometimes after starting treatment with antibiotics, patients can develop watery and bloody stools (with or without stomach cramps and fever) even as late as 2 or more months after having taken the last dose of the antibiotic. If this occurs, patients should contact their physician as soon as possible.

Keep suspension refrigerated. Shake well before using. When dosing a child with the suspension (liquid) of Amoxicillin and Clavulanate Potassium, use a dosing spoon or medicine dropper. Be sure to rinse the spoon or dropper after each use. Bottles of suspension of Amoxicillin and Clavulanate Potassium may contain more liquid than required. Follow your doctor’s instructions about the amount to use and the days of treatment your child requires. Discard any unused medicine.

Patients should be counseled that antibacterial drugs including Amoxicillin and Clavulanate Potassium, should only be used to treat bacterial infections. They do not treat viral infections (e.g., the common cold). When Amoxicillin and Clavulanate Potassium is prescribed to treat a bacterial infection, patients should be told that although it is common to feel better early in the course of therapy, the medication should be taken exactly as directed. Skipping doses or not completing the full course of therapy may: (1) decrease the effectiveness of the immediate treatment, and (2) increase the likelihood that bacteria will develop resistance and will not be treatable by Amoxicillin and Clavulanate Potassium or other antibacterial drugs in the future.

Phenylketonurics:

Each 200 mg/28.5 mg chewable tablet of Amoxicillin and Clavulanate Potassium contains 2.1 mg phenylalanine; each 400 mg/57 mg chewable tablet contains 4.2 mg phenylalanine; each 5 mL of either the 200 mg/28.5 mg per 5 mL or 400 mg/57 mg per 5 mL oral suspension contains 7 mg phenylalanine. The other products of Amoxicillin and Clavulanate Potassium do not contain phenylalanine and can be used by phenylketonurics. Contact your physician or pharmacist.

Drug Interactions:

Probenecid decreases the renal tubular secretion of amoxicillin. Concurrent use with Amoxicillin and Clavulanate Potassium may result in increased and prolonged blood levels of amoxicillin. Coadministration of probenecid cannot be recommended.

Abnormal prolongation of prothrombin time (increased international normalized ratio [INR]) has been reported rarely in patients receiving amoxicillin and oral anticoagulants. Appropriate monitoring should be undertaken when anticoagulants are prescribed concurrently. Adjustments in the dose of oral anticoagulants may be necessary to maintain the desired level of anticoagulation.

The concurrent administration of allopurinol and ampicillin increases substantially the incidence of rashes in patients receiving both drugs as compared to patients receiving ampicillin alone. It is not known whether this potentiation of ampicillin rashes is due to allopurinol or the hyperuricemia present in these patients. There are no data with Amoxicillin and Clavulanate Potassium and allopurinol administered concurrently.

In common with other broad-spectrum antibiotics, Amoxicillin and Clavulanate Potassium may reduce the efficacy of oral contraceptives.

Drug/Laboratory Test Interactions:

Oral administration of Amoxicillin and Clavulanate Potassium will result in high urine concentrations of amoxicillin. High urine concentrations of ampicillin may result in false-positive reactions when testing for the presence of glucose in urine using CLINITEST®, Benedict’s Solution, or Fehling’s Solution. Since this effect may also occur with amoxicillin and therefore Amoxicillin and Clavulanate Potassium, it is recommended that glucose tests based on enzymatic glucose oxidase reactions (such as CLINISTIX®) be used.

Following administration of ampicillin to pregnant women, a transient decrease in plasma concentration of total conjugated estriol, estriol-glucuronide, conjugated estrone, and estradiol has been noted. This effect may also occur with amoxicillin and therefore Amoxicillin and Clavulanate Potassium.

Carcinogenesis, Mutagenesis, Impairment of Fertility:

Long-term studies in animals have not been performed to evaluate carcinogenic potential.

Mutagenesis:

The mutagenic potential of Amoxicillin and Clavulanate Potassium was investigated in vitro with an Ames test, a human lymphocyte cytogenetic assay, a yeast test and a mouse lymphoma forward mutation assay, and in vivo with mouse micronucleus tests and a dominant lethal test. All were negative apart from the in vitro mouse lymphoma assay where weak activity was found at very high, cytotoxic concentrations.

Impairment of Fertility:

Amoxicillin and Clavulanate Potassium at oral doses of up to 1,200 mg/kg/day (5.7 times the maximum human dose, 1,480 mg/m^2/day, based on body surface area) was found to have no effect on fertility and reproductive performance in rats, dosed with a 2:1 ratio formulation of amoxicillin:clavulanate.

Pregnancy:

Teratogenic Effects:

Pregnancy (Category B). Reproduction studies performed in pregnant rats and mice given Amoxicillin and Clavulanate Potassium at oral dosages up to 1,200 mg/kg/day, equivalent to 7,200 and 4,080 mg/m^2/day, respectively (4.9 and 2.8 times the maximum human oral dose based on body surface area), revealed no evidence of harm to the fetus due to Amoxicillin and Clavulanate Potassium. There are, however, no adequate and well-controlled studies in pregnant women. Because animal reproduction studies are not always predictive of human response, this drug should be used during pregnancy only if clearly needed.

Labor and Delivery:

Oral ampicillin-class antibiotics are generally poorly absorbed during labor. Studies in guinea pigs have shown that intravenous administration of ampicillin decreased the uterine tone, frequency of contractions, height of contractions, and duration of contractions. However, it is not known whether the use of Amoxicillin and Clavulanate Potassium in humans during labor or delivery has immediate or delayed adverse effects on the fetus, prolongs the duration of labor, or increases the likelihood that forceps delivery or other obstetrical intervention or resuscitation of the newborn will be necessary. In a single study in women with premature rupture of fetal membranes, it was reported that prophylactic treatment with Amoxicillin and Clavulanate Potassium may be associated with an increased risk of necrotizing enterocolitis in neonates.

Nursing Mothers:

Ampicillin-class antibiotics are excreted in the milk; therefore, caution should be exercised when Amoxicillin and Clavulanate Potassium is administered to a nursing woman.

Pediatric Use:

Because of incompletely developed renal function in neonates and young infants, the elimination of amoxicillin may be delayed. Dosing of Amoxicillin and Clavulanate Potassium should be modified in pediatric patients younger than 12 weeks (3 months). (See DOSAGE AND ADMINISTRATION—Pediatric.)

ADVERSE REACTIONS

Amoxicillin and Clavulanate Potassium is generally well tolerated. The majority of side effects observed in clinical trials were of a mild and transient nature and less than 3% of patients discontinued therapy because of drug-related side effects. From the original premarketing studies, where both pediatric and adult patients were enrolled, the most frequently reported adverse effects were diarrhea/loose stools (9%), nausea (3%), skin rashes and urticaria (3%), vomiting (1%) and vaginitis (1%). The overall incidence of side effects, and in particular diarrhea, increased with the higher recommended dose. Other less frequently reported reactions include: Abdominal discomfort, flatulence, and headache.

In pediatric patients (aged 2 months to 12 years), 1 US/Canadian clinical trial was conducted which compared 45/6.4 mg/kg/day (divided every 12 hours) of Amoxicillin and Clavulanate Potassium for 10 days versus 40/10 mg/kg/day (divided every 8 hours) of Amoxicillin and Clavulanate Potassium for 10 days in the treatment of acute otitis media. A total of 575 patients were enrolled, and only the suspension formulations were used in this trial. Overall, the adverse event profile seen was comparable to that noted above; however, there were differences in the rates of diarrhea, skin rashes/urticaria, and diaper area rashes. (See CLINICAL STUDIES.)

The following adverse reactions have been reported for ampicillin-class antibiotics:

Gastrointestinal:

Diarrhea, nausea, vomiting, indigestion, gastritis, stomatitis, glossitis, black “hairy” tongue, mucocutaneous candidiasis, enterocolitis, and hemorrhagic/pseudomembranous colitis. Onset of pseudomembranous colitis symptoms may occur during or after antibiotic treatment. (See WARNINGS.)

Hypersensitivity Reactions:

Skin rashes, pruritus, urticaria, angioedema, serum sickness−like reactions (urticaria or skin rash accompanied by arthritis, arthralgia, myalgia, and frequently fever), erythema multiforme (rarely Stevens-Johnson syndrome), acute generalized exanthematous pustulosis, hypersensitivity vasculitis, and an occasional case of exfoliative dermatitis (including toxic epidermal necrolysis) have been reported. These reactions may be controlled with antihistamines and, if necessary, systemic corticosteroids. Whenever such reactions occur, the drug should be discontinued, unless the opinion of the physician dictates otherwise. Serious and occasional fatal hypersensitivity (anaphylactic) reactions can occur with oral penicillin. (See WARNINGS.)

Liver:

A moderate rise in AST (SGOT) and/or ALT (SGPT) has been noted in patients treated with ampicillin-class antibiotics, but the significance of these findings is unknown. Hepatic dysfunction, including hepatitis and cholestatic jaundice, (see CONTRAINDICATIONS), increases in serum transaminases (AST and/or ALT), serum bilirubin and/or alkaline phosphatase, has been infrequently reported with Amoxicillin and Clavulanate Potassium. It has been reported more commonly in the elderly, in males, or in patients on prolonged treatment. The histologic findings on liver biopsy have consisted of predominantly cholestatic, hepatocellular, or mixed cholestatic-hepatocellular changes. The onset of signs/symptoms of hepatic dysfunction may occur during or several weeks after therapy has been discontinued. The hepatic dysfunction, which may be severe, is usually reversible. On rare occasions, deaths have been reported (less than 1 death reported per estimated 4 million prescriptions worldwide). These have generally been cases associated with serious underlying diseases or concomitant medications.

Renal:

Interstitial nephritis and hematuria have been reported rarely. Crystalluria has also been reported (see OVERDOSAGE).

Hemic and Lymphatic Systems:

Anemia, including hemolytic anemia, thrombocytopenia, thrombocytopenic purpura, eosinophilia, leukopenia, and agranulocytosis have been reported during therapy with penicillins. These reactions are usually reversible on discontinuation of therapy and are believed to be hypersensitivity phenomena. A slight thrombocytosis was noted in less than 1% of the patients treated with Amoxicillin and Clavulanate Potassium. There have been reports of increased prothrombin time in patients receiving Amoxicillin and Clavulanate Potassium and anticoagulant therapy concomitantly.

Central Nervous System:

Agitation, anxiety, behavioral changes, confusion, convulsions, dizziness, insomnia, and reversible hyperactivity have been reported rarely.

Miscellaneous:

Tooth discoloration (brown, yellow, or gray staining) has been rarely reported. Most reports occurred in pediatric patients. Discoloration was reduced or eliminated with brushing or dental cleaning in most cases.

OVERDOSAGE

Following overdosage, patients have experienced primarily gastrointestinal symptoms including stomach and abdominal pain, vomiting, and diarrhea. Rash, hyperactivity, or drowsiness have also been observed in a small number of patients.

In the case of overdosage, discontinue Amoxicillin and Clavulanate Potassium, treat symptomatically, and institute supportive measures as required. If the overdosage is very recent and there is no contraindication, an attempt at emesis or other means of removal of drug from the stomach may be performed. A prospective study of 51 pediatric patients at a poison center suggested that overdosages of less than 250 mg/kg of amoxicillin are not associated with significant clinical symptoms and do not require gastric emptying.^3

Interstitial nephritis resulting in oliguric renal failure has been reported in a small number of patients after overdosage with amoxicillin.

Crystalluria, in some cases leading to renal failure, has also been reported after amoxicillin overdosage in adult and pediatric patients. In case of overdosage, adequate fluid intake and diuresis should be maintained to reduce the risk of amoxicillin crystalluria.

Renal impairment appears to be reversible with cessation of drug administration. High blood levels may occur more readily in patients with impaired renal function because of decreased renal clearance of both amoxicillin and clavulanate. Both amoxicillin and clavulanate are removed from the circulation by hemodialysis.

DOSAGE AND ADMINISTRATION

Pediatric Patients:

Based on the amoxicillin component, Amoxicillin and Clavulanate Potassium should be dosed as follows:

Neonates and infants aged < 12 weeks (3 months):

Due to incompletely developed renal function affecting elimination of amoxicillin in this age group, the recommended dose of Amoxicillin and Clavulanate Potassium is 30 mg/kg/day divided every 12 hours, based on the amoxicillin component. Clavulanate elimination is unaltered in this age group. Experience with the 200 mg/28.5 mg per 5 mL formulation in this age group is limited and, thus, use of the 125 mg/31.25 mg per 5 mL oral suspension is recommended.

Patients aged 12 weeks (3 months) and older

INFECTIONS | DOSING REGIMEN
INFECTIONS | q12ha | q8h
 | 200 mg/28.5 mg per 5 mL or 400 mg/57 mg per 5 mL oral suspensionb | 125 mg/31.25 mg per 5 mL or 250 mg/62.5 mg per 5 mL oral suspension
Otitis mediac, sinusitis, lower respiratory tract infections, and more severe infections | 45 mg/kg/day q12h | 40 mg/kg/day q8h
Less severe infections | 25 mg/kg/day q12h | 20 mg/kg/day q8h

a The q12h regimen is recommended as it is associated with significantly less diarrhea. (See CLINICAL STUDIES.) However, the q12h formulations (200 mg and 400 mg) contain aspartame and should not be used by phenylketonurics.

b Each strength of suspension of Amoxicillin and Clavulanate Potassium is available as a chewable tablet for use by older children.

c Duration of therapy studied and recommended for acute otitis media is 10 days.

Pediatric Patients Weighing 40 kg and More:

Should be dosed according to the following adult recommendations: The usual adult dose is one 500 mg/125 mg tablet of Amoxicillin and Clavulanate Potassium every 12 hours or one 250 mg/125 mg tablet of Amoxicillin and Clavulanate Potassium every 8 hours. For more severe infections and infections of the respiratory tract, the dose should be one 875 mg/125 mg tablet of Amoxicillin and Clavulanate Potassium every 12 hours or one 500 mg/125 mg tablet of Amoxicillin and Clavulanate Potassium every 8 hours. Among adults treated with 875 mg/125 mg every 12 hours, significantly fewer experienced severe diarrhea or withdrawals with diarrhea versus adults treated with 500 mg/125 mg every 8 hours. For detailed adult dosage recommendations, please see complete prescribing information for tablets of Amoxicillin and Clavulanate Potassium.

Hepatically impaired patients should be dosed with caution and hepatic function monitored at regular intervals. (See WARNINGS.)

Adults:

Adults who have difficulty swallowing may be given the 125 mg/31.25 mg per 5 mL or 250 mg/62.5 mg per 5 mL suspension in place of the 500 mg/125 mg tablet. The 200 mg/28.5 mg per 5 mL suspension or the 400 mg/57 mg per 5 mL suspension may be used in place of the 875 mg/125 mg tablet. See dosage recommendations above for children weighing 40 kg or more.

The 250 mg/125 mg tablet of Amoxicillin and Clavulanate Potassium and the 250 mg/62.5 mg chewable tablet do not contain the same amount of clavulanic acid (as the potassium salt). The 250 mg/125 mg tablet of Amoxicillin and Clavulanate Potassium contains 125 mg of clavulanic acid, whereas the 250 mg/62.5 mg chewable tablet contains 62.5 mg of clavulanic acid. Therefore, the 250 mg/125 mg tablet of Amoxicillin and Clavulanate Potassium and the 250 mg/62.5 mg chewable tablet should not be substituted for each other, as they are not interchangeable.

Due to the different amoxicillin to clavulanic acid ratios in the 250 mg/125 mg tablet of Amoxicillin and Clavulanate Potassium (250/125) versus the 250 mg/62.5 mg chewable tablet of Amoxicillin and Clavulanate Potassium (250/62.5), the 250 mg/125 mg tablet of Amoxicillin and Clavulanate Potassium should not be used until the child weighs at least 40 kg and more.

Directions for Mixing Oral Suspension:

Prepare a suspension at time of dispensing as follows: Tap bottle until all the powder flows freely. Add approximately 2/3 of the total amount of water for reconstitution (see table below) and shake vigorously to suspend powder. Add remainder of the water and again shake vigorously.

Amoxicillin and Clavulanate Potassium 125 mg/31.25 mg per 5 mL Suspension
Bottle Size | Amount of Water; Required for Reconstitution
75 mL | 67 mL
100 mL | 90 mL
150 mL | 134 mL

Each teaspoonful (5 mL) will contain 125 mg amoxicillin and 31.25 mg of clavulanic acid as the potassium salt.

Amoxicillin and Clavulanate Potassium 200 mg/28.5 mg per 5 mL Suspension
Bottle Size | Amount of Water; Required for Reconstitution
50 mL | 50 mL
75 mL | 75 mL
100 mL | 95 mL

Each teaspoonful (5 mL) will contain 200 mg amoxicillin and 28.5 mg of clavulanic acid as the potassium salt.

Amoxicillin and Clavulanate Potassium 250 mg/62.5 mg per 5 mL Suspension
Bottle Size | Amount of Water; Required for Reconstitution
75 mL | 65 mL
100 mL | 87 mL
150 mL | 130 mL

Each teaspoonful (5 mL) will contain 250 mg amoxicillin and 62.5 mg of clavulanic acid as the potassium salt.

Amoxicillin and Clavulanate Potassium 400 mg/57 mg per 5 mL Suspension
Bottle Size | Amount of Water; Required for Reconstitution
50 mL | 50 mL
75 mL | 70 mL
100 mL | 90 mL

Each teaspoonful (5 mL) will contain 400 mg amoxicillin and 57.0 mg of clavulanic acid as the potassium salt.

Note: SHAKE ORAL SUSPENSION WELL BEFORE USING.

Reconstituted suspension must be stored under refrigeration and discarded after 10 days.

Administration:

Amoxicillin and Clavulanate Potassium may be taken without regard to meals; however, absorption of clavulanate potassium is enhanced when Amoxicillin and Clavulanate Potassium is administered at the start of a meal. To minimize the potential for gastrointestinal intolerance, Amoxicillin and Clavulanate Potassium should be taken at the start of a meal.

HOW SUPPLIED

Amoxicillin and Clavulanate Potassium 400 mg/57 mg per 5 mL for Oral Suspension: Each 5 mL of reconstituted orange-flavored suspension contains 400 mg amoxicillin and 57 mg clavulanic acid as the potassium salt.

NDC 42254-282-00 100 mL bottle

Store tablets and dry powder at or below 25°C (77°F). Dispense in original containers. Store reconstituted suspension under refrigeration. Discard unused suspension after 10 days.

CLINICAL STUDIES

In pediatric patients (aged 2 months to 12 years), 1 US/Canadian clinical trial was conducted which compared 45/6.4 mg/kg/day (divided every 12 hours) of Amoxicillin and Clavulanate Potassium for 10 days versus 40/10 mg/kg/day (divided every 8 hours) of Amoxicillin and Clavulanate Potassium for 10 days in the treatment of acute otitis media. Only the suspension formulations were used in this trial. A total of 575 patients were enrolled, with an even distribution among the 2 treatment groups and a comparable number of patients were evaluable (i.e., ≥ 84%) per treatment group. Strict otitis media-specific criteria were required for eligibility and a strong correlation was found at the end of therapy and follow-up between these criteria and physician assessment of clinical response. The clinical efficacy rates at the end of therapy visit (defined as 2-4 days after the completion of therapy) and at the follow-up visit (defined as 22-28 days post-completion of therapy) were comparable for the 2 treatment groups, with the following cure rates obtained for the evaluable patients: At end of therapy, 87.2% (n = 265) and 82.3% (n = 260) for 45 mg/kg/day every 12 hours and 40 mg/kg/day every 8 hours, respectively. At follow-up, 67.1% (n = 249) and 68.7% (n = 243) for 45 mg/kg/day every 12 hours and 40 mg/kg/day every 8 hours, respectively.

The incidence of diarrheaa was significantly lower in patients in the every 12 hours treatment group compared to patients who received the every 8 hours regimen (14.3% and 34.3%, respectively). In addition, the number of patients with either severe diarrhea or who were withdrawn with diarrhea was significantly lower in the every 12 hours treatment group (3.1% and 7.6% for the every 12 hours/10 day and every 8 hours/10 day, respectively). In the every 12 hours treatment group, 3 patients (1.0%) were withdrawn with an allergic reaction, while 1 patient (0.3%) in the every 8 hours group was withdrawn for this reason. The number of patients with a candidal infection of the diaper area was 3.8% and 6.2% for the every 12 hours and every 8 hours groups, respectively.

It is not known if the finding of a statistically significant reduction in diarrhea with the oral suspensions dosed every 12 hours, versus suspensions dosed every 8 hours, can be extrapolated to the chewable tablets. The presence of mannitol in the chewable tablets may contribute to a different diarrhea profile. The every 12 hours oral suspensions are sweetened with aspartame only.

a Diarrhea was defined as either: (a) 3 or more watery or 4 or more loose/watery stools in 1 day; OR (b) 2 watery stools per day or 3 loose/watery stools per day for 2 consecutive days.

REFERENCES

1. Clinical and Laboratory Standards Institute (CLSI). Methods for Dilution Antimicrobial Susceptibility Tests for Bacteria That Grow Aerobically; Approved Standard – 8th ed. CLSI Document M07-A8. CLSI, 940 West Valley Rd., Suite 1400, Wayne, PA 19087, 2009.
2. Clinical and Laboratory Standards Institute (CLSI). Performance Standards for Antimicrobial Disk Susceptibility Test; Approved Standard – 10th ed. CLSI Document M02-A10. CLSI, 940 West Valley Rd., Suite 1400, Wayne, PA 19087, 2009.
3. Swanson-Biearman B, Dean BS, Lopez G, Krenzelok EP. The effects of penicillin and cephalosporin ingestions in children less than six years of age. Vet Hum Toxicol 1988;30:66-67.

CLINITEST is a registered trademark of Miles, Inc.

CLINISTIX is a registered trademark of Bayer Corporation.

Manufactured by:

Dr. Reddy's Laboratories Inc.

Bridgewater, NJ 08807

Repackaged by:

Rebel Distributors Corp.

Thousand Oaks, CA 91320